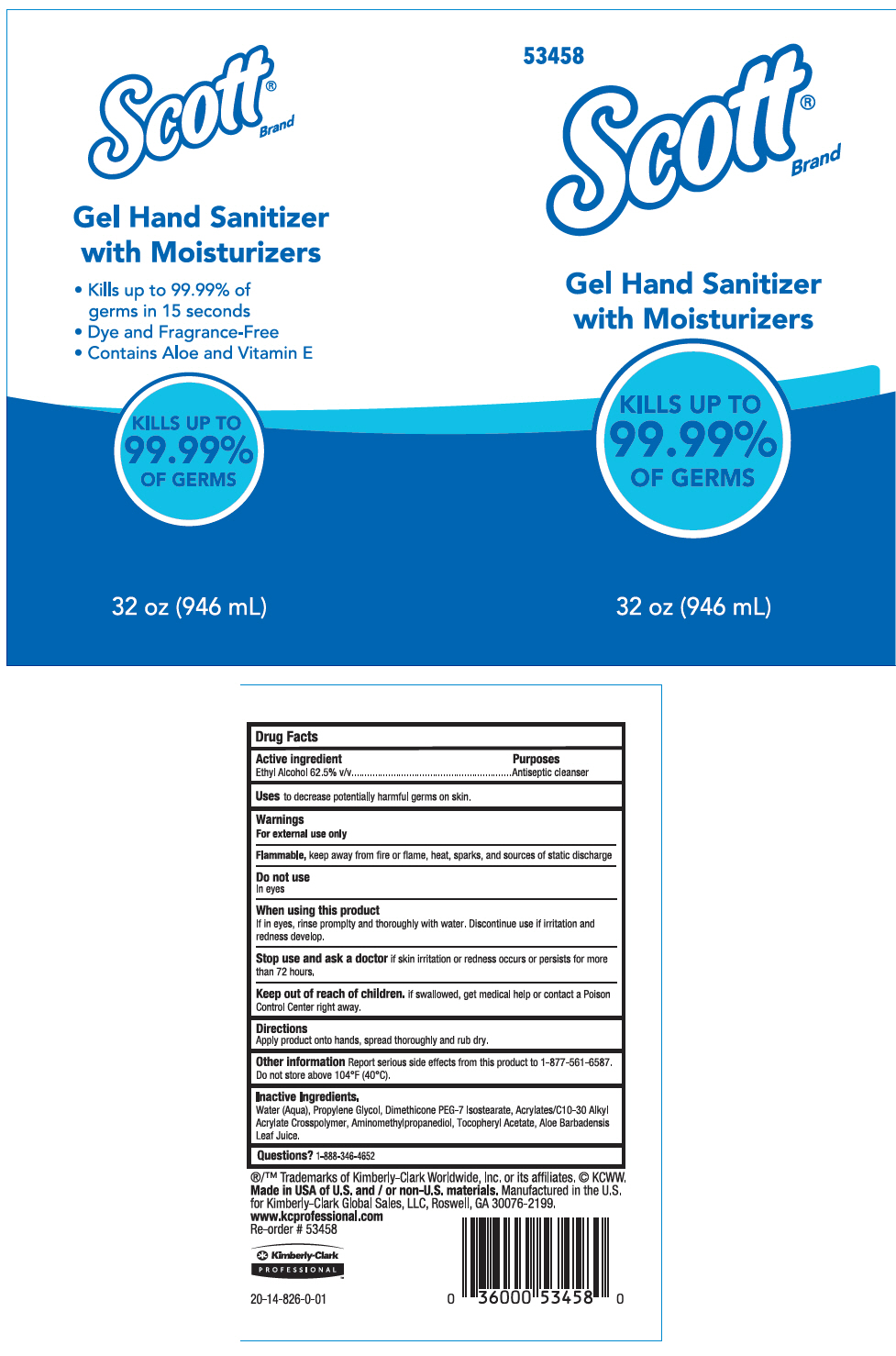 DRUG LABEL: Scott Gel Hand Sanitizer with Moisturizers
NDC: 55118-702 | Form: GEL
Manufacturer: Kimberly-Clark
Category: otc | Type: HUMAN OTC DRUG LABEL
Date: 20210722

ACTIVE INGREDIENTS: ALCOHOL 62.5 mL/100 mL
INACTIVE INGREDIENTS: WATER; ALOE VERA LEAF; PROPYLENE GLYCOL; AMINOMETHYLPROPANOL; DIMETHICONE PEG-7 ISOSTEARATE; CARBOMER INTERPOLYMER TYPE A (ALLYL SUCROSE CROSSLINKED)

Hand Sanitizer

Drug Facts

Active ingredient

Ethyl Alcohol 62.5% v/v.

Purposes

Antiseptic cleanser

Uses

to decrease potentially harmful germs on skin.

Warnings

For external use only

Flammable, keep away from fire or flame, heat, sparks, and sources of static discharge

Do not use

In eyes

When using this product

If in eyes, rinse promplty and thoroughly with water. Discontinue use if irritation and redness develop.

Stop use and ask a doctor if skin irritation or redness occurs or persists for more than 72 hours.

Keep out of reach of children. if swallowed, get medical help or contact a Poison Control Center right away.

Directions

Apply product onto hands, spread thoroughly and rub dry.

Other information

Report serious side effects from this product to 1-877-561-6587. Do not store above 104°F (40°C).

Inactive Ingredients

Water (Aqua), Propylene Glycol, Dimethicone PEG-7 Isostearate, Acrylates/C10-30 Alkyl Acrylate Crosspolymer, Aminomethylpropanediol, Tocopheryl Acetate, Aloe Barbadensis Leaf Juice.

Questions?

1-888-346-4652

PRINCIPAL DISPLAY PANEL - 946 mL Bottle Label

53458

Scott®
Brand

Gel Hand Sanitizer
with Moisturizers

KILLS UP TO
99.99%
OF GERMS

32 oz (946 mL)